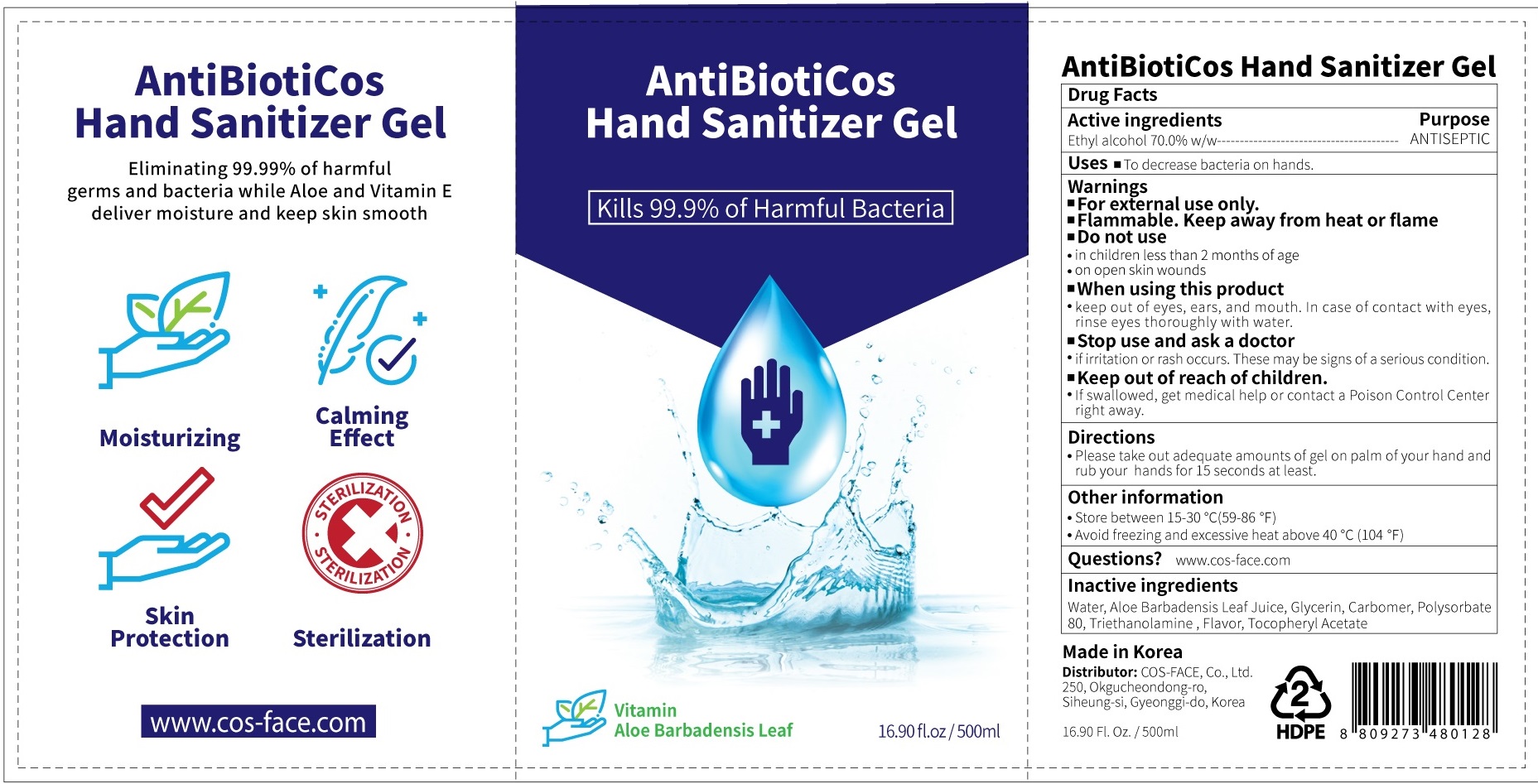 DRUG LABEL: AntiBiotiCos Hand Sanitizer
NDC: 75008-010 | Form: GEL
Manufacturer: COS-FACE Co., Ltd.
Category: otc | Type: HUMAN OTC DRUG LABEL
Date: 20200419

ACTIVE INGREDIENTS: ALCOHOL 350 g/500 mL
INACTIVE INGREDIENTS: Water; ALOE VERA LEAF; Glycerin; CARBOMER HOMOPOLYMER, UNSPECIFIED TYPE; Polysorbate 80; TROLAMINE; .ALPHA.-TOCOPHEROL ACETATE

Active Ingredients

Active ingredients: Ethyl alcohol 70.0% w/w

INACTIVE INGREDIENT

Inactive ingredients:

Water, Aloe Barbadensis Leaf Juice, Glycerin, Carbomer, Polysorbate 80, Triethanolamine , Flavor, Tocopheryl Acetate

Purpose

Purpose: ANTISEPTIC

Warnings

■For external use only.
■Flammable. Keep away from heat or flame
■Do not use
• in children less than 2 months of age
• on open skin wounds
■When using this product
• keep out of eyes, ears, and mouth. In case of contact with eyes, rinse eyes thoroughly with water.
■Stop use and ask a doctor
• if irritation or rash occurs. These may be signs of a serious condition.

Keep out of reach of children. If swallowed, get medical help or contact a Poison Control Center right away.

Uses

To decrease bacteria on hands.

Directions

Please take out adequate amounts of gel on palm of your hand and rub your hands for 15 seconds at least.

Other information

• Store between 15-30˚C (59-86˚F)
• Avoid freezing and excessive heat above 40˚C (104˚F)

Questions

www.cos-face.com